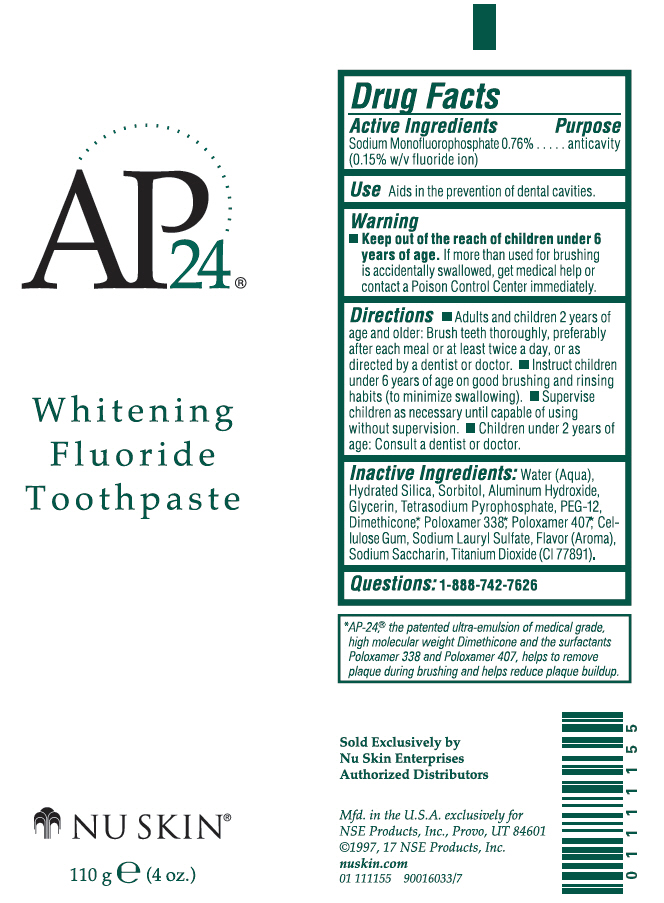 DRUG LABEL: AP-24 Whitening
NDC: 62839-1155 | Form: PASTE
Manufacturer: NSE Products, Inc.
Category: otc | Type: HUMAN OTC DRUG LABEL
Date: 20250106

ACTIVE INGREDIENTS: Sodium Monofluorophosphate 7.6 mg/1 g
INACTIVE INGREDIENTS: Water; Hydrated Silica; Sorbitol; Aluminum Hydroxide; Glycerin; Sodium Pyrophosphate; Polyethylene Glycol 600; Dimethicone; Poloxamer 338; Poloxamer 407; CARBOXYMETHYLCELLULOSE SODIUM, UNSPECIFIED; Sodium Lauryl Sulfate; Saccharin Sodium; Titanium Dioxide

AP-24® Whitening Toothpaste

Drug Facts

Active Ingredients

Sodium Monofluorophosphate 0.76% (0.15% w/v fluoride ion)

Purpose

anticavity

Use

Aids in the prevention of dental cavities.

Warning

KEEP OUT OF REACH OF CHILDREN

- Keep out of the reach of children under 6 years of age. If more than used for brushing is accidentally swallowed, get medical help or contact a Poison Control Center immediately.

Directions

- Adults and children 2 years of age and older: Brush teeth thoroughly, preferably after each meal or at least twice a day, or as directed by a dentist or doctor.
- Instruct children under 6 years of age on good brushing and rinsing habits (to minimize swallowing).
- Supervise children as necessary until capable of using without supervision.
- Children under 2 years of age: Consult a dentist or doctor.

Inactive Ingredients

Water (Aqua), Hydrated Silica, Sorbitol, Alumina, Glycerin, Tetrasodium Pyrophosphate, PEG-12, Dimethicone [AP-24,® the patented ultra-emulsion of medical grade, high molecular weight Dimethicone and the surfactants Poloxamer 338 and Poloxamer 407, helps to remove plaque during brushing and helps reduce plaque buildup.] , Poloxamer 338, Poloxamer 407, Cellulose Gum, Sodium Lauryl Sulfate, Flavor (Aroma), Sodium Saccharin, Titanium Dioxide (CI 77891).

Questions

1-888-742-7626

PRINCIPAL DISPLAY PANEL - 110 g Tube Label

AP24®

Whitening
Fluoride
Toothpaste

NU SKIN®

110 g e (4 oz.)